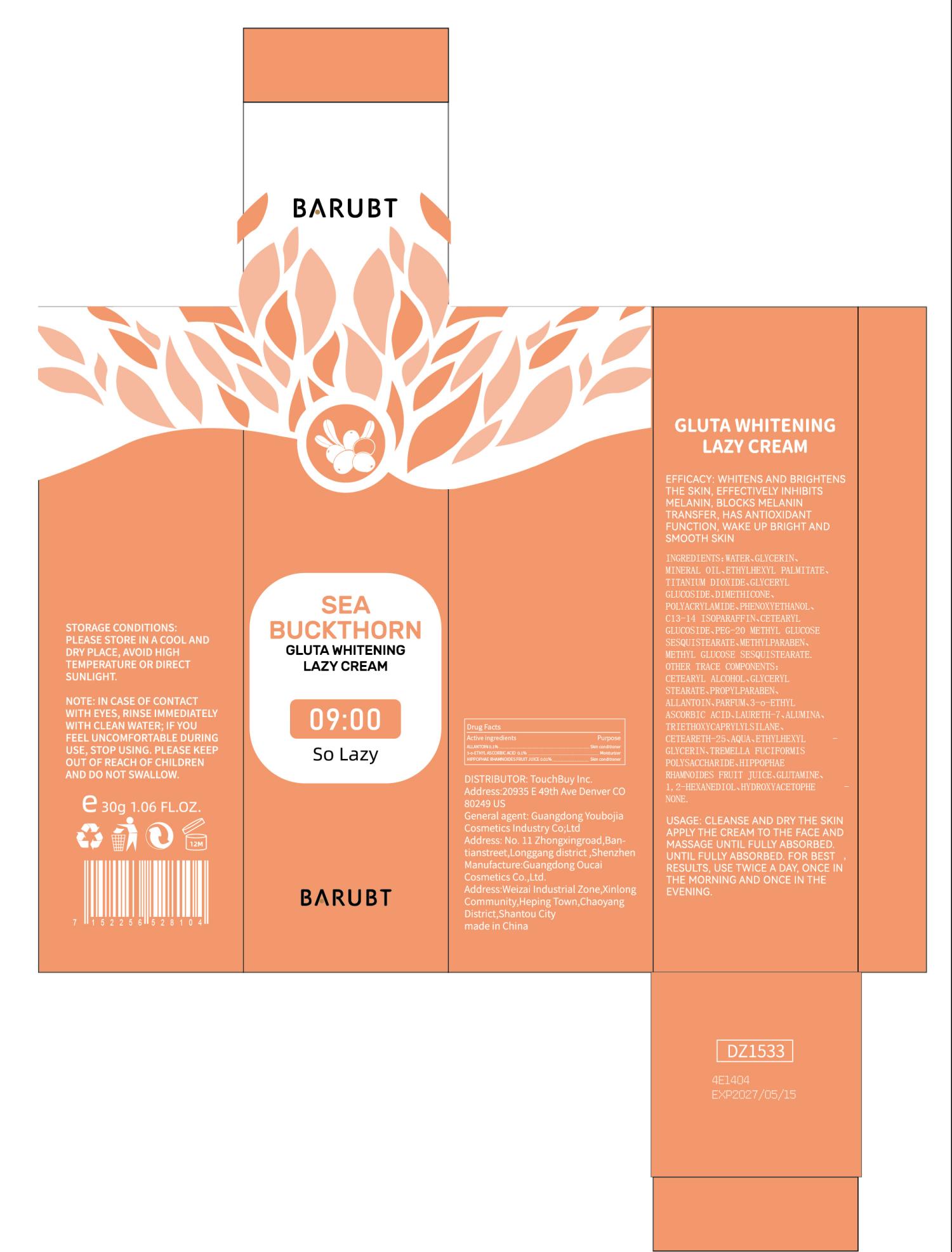 DRUG LABEL: BARUBT Gluta Whitening Lazy Cream
NDC: 84712-033 | Form: CREAM
Manufacturer: Guangdong Youbaijia Cosmetic Industry Co., Ltd
Category: otc | Type: HUMAN OTC DRUG LABEL
Date: 20241127

ACTIVE INGREDIENTS: 3-O-ETHYL ASCORBIC ACID 0.03 g/30 g; ALLANTOIN 0.03 g/30 g; HIPPOPHAE RHAMNOIDES FRUIT JUICE 0.003 g/30 g
INACTIVE INGREDIENTS: MINERAL OIL 1.2 g/30 g

ACTIVE INGREDIENT

ALLANTOIN 0.1%
3-o-ETHYL ASCORBIC ACID 0.1%
HIPPOPHAE RHAMNOIDES FRUIT JUICE 0.01%

INACTIVE INGREDIENT

WATER. GLYCERIN, MINERAL OIL, ETHYLHEXYL PALMITATE, TITANIUM DIOXIDE. GLYCERYL GLUCOSIDE.DIMETHICONE, POLYACRYLAMIDE, PHENOXYETHANOL, C13-14 ISOPARAFFIN. CETEARYL GLUCOSIDE, PEG-20 METHYL GLUCOSE SESQUISTEARATE. METHYLPARABEN, METHYL GLUCOSE SESQUISTEARATE. CETEARYL ALCOHOL, GLYCERYL STEARATE, PROPYLPARABEN. PARFUM, LAURETH-7, ALUMINA. TRIETHOXYCAPRYLYLSILANE. CETEARETH-25, AQUA. ETHYLHEXYLGLYCERIN. TREMELLA FUCIFORMIS POLYSACCHARIDE, GLUTAMINE. 1,2-HEXANEDIOL, HYDROXYACETOPHENONE.

DO NOT USE

on damaged or broken skin

Keep away from children. Do not swallow.

PURPOSE

WHITENS AND BRIGHTENS THE SKIN

QUESTIONS

Contact name: Jessie Peng
Company phone number: +1 818 579 7288
Company e-mail: jessie@registeragentllc.com

STOP USE

lf skin becomes red or irritated, discontinue use immediately and wash with water.

WHEN USING

keep out of eyes. Rinse with water to remove.

INDICATIONS AND USAGE

WHITENS AND BRIGHTENS THE SKIN, EFFECTIVELY INHIBITS MELANIN, BLOCKS MELANIN TRANSFER, HAS ANTIOXIDANT FUNCTION, WAKE UP BRIGHT AND SMOOTH SKIN

DOSAGE AND ADMINISTRATION

CLEANSE AND DRY THE SKIN APPLY THE CREAM TO THE FACE AND MASSAGE UNTIL FULLY ABSORBED. UNTIL FULLY ABSORBED. FOR BEST RESULTS, USE TWICE A DAY, ONCE IN THE MORNING AND ONCE IN THE EVENING.

WARNINGS

For external use only.

STORAGE AND HANDLING

Keep away from light and in a dry place.